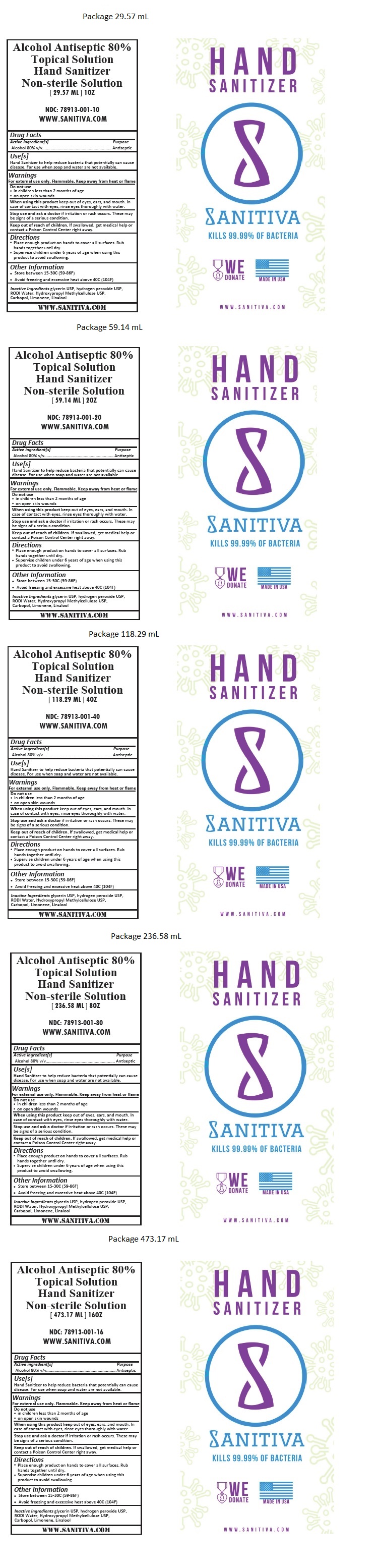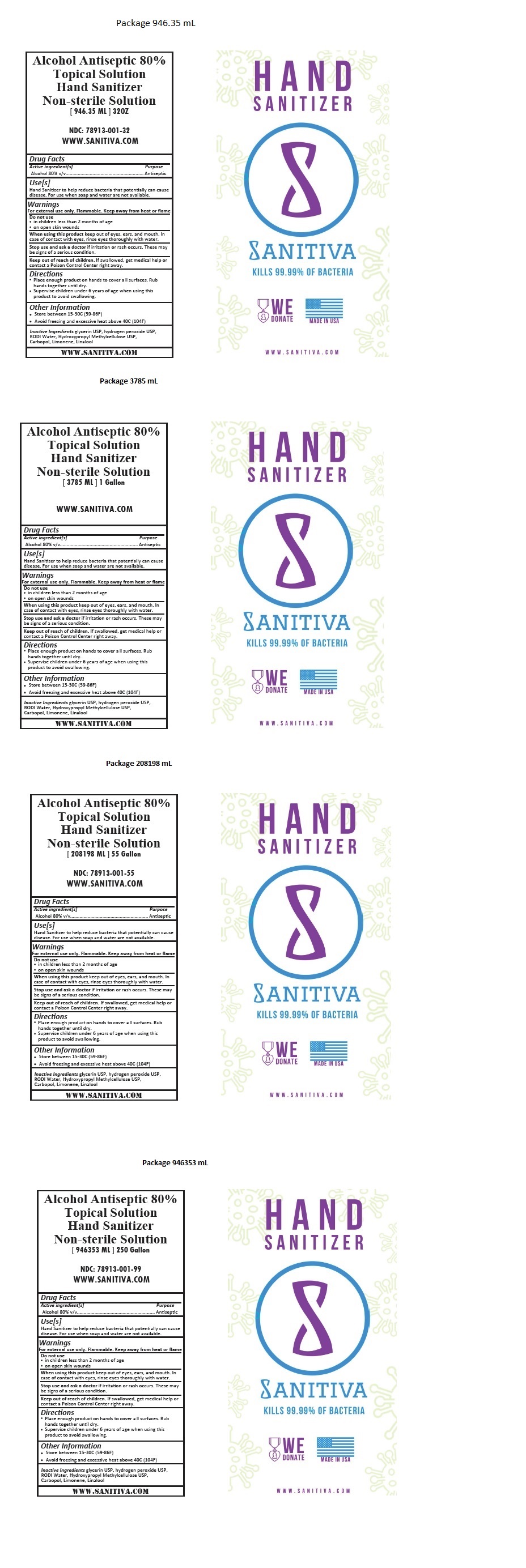 DRUG LABEL: SANITIVA HAND SANITIZER
NDC: 78913-001 | Form: SOLUTION
Manufacturer: Alpha Extractors, LLC
Category: otc | Type: HUMAN OTC DRUG LABEL
Date: 20200730

ACTIVE INGREDIENTS: ALCOHOL 80 mL/100 mL
INACTIVE INGREDIENTS: GLYCERIN; HYDROGEN PEROXIDE; WATER; HYPROMELLOSE, UNSPECIFIED; CARBOMER HOMOPOLYMER, UNSPECIFIED TYPE; LIMONENE, (+)-; LINALOOL, (+/-)-

SANITIVA HAND SANITIZER

Active ingredient[s]

Alcohol 80% v/v

Purpose

Antiseptic

Use[s]

Hand Sanitizer to help reduce bacteria that potentially can cause disease. For use when soap and water are not available.

Warnings

For external use only. Flammable. Keep away from heat or flame

Do not use

- in children less than 2 months of age
- on open skin wounds

When using this product keep out of eyes, ears, and mouth. In case of contact with eyes, rinse eyes thoroughly with water.

Stop use and ask a doctor if irritation or rash occurs. These may be signs of a serious condition.

Keep out of reach of children. If swallowed, get medical help or contact a Poison Control Center right away.

Directions

- Place enough product on hands to cover all surfaces. Rub hands together until dry.
- Supervise children under 6 years of age when using this product to avoid swallowing.

Other Information

- Store between 15-30C (59-86F)
- Avoid freezing and excessive heat above 40C (104F)

INACTIVE INGREDIENT

Inactive Ingredients glycerin USP, hydrogen peroxide USP, RODI Water, Hydroxypropyl Methylcellulose USP, Carbopol, Limonene, Linalool

KILLS 99.99% OF BACTERIA

WE DONATE

MADE IN USA

WWW.SANITIVA.COM

Alcohol Antiseptic 80%
Topical Solution
Hand Sanitizer
Non-sterile Solution